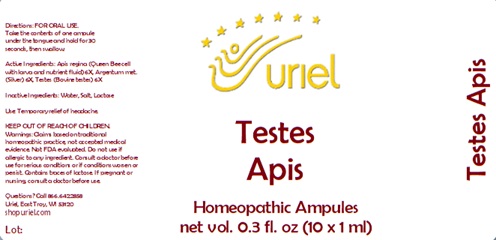 DRUG LABEL: Testes Apis
NDC: 48951-9001 | Form: LIQUID
Manufacturer: Uriel Pharmacy Inc.
Category: homeopathic | Type: HUMAN OTC DRUG LABEL
Date: 20231204

ACTIVE INGREDIENTS: ROYAL JELLY 6 [hp_X]/1 mL; SILVER 6 [hp_X]/1 mL; BOS TAURUS TESTICLE 6 [hp_X]/1 mL
INACTIVE INGREDIENTS: WATER; SODIUM CHLORIDE; LACTOSE

Testes Apis

INDICATIONS AND USAGE

Directions: FOR ORAL USE.

DOSAGE AND ADMINISTRATION

Take the contents of one ampule under the tongue and hold for 30 seconds, then swallow.

ACTIVE INGREDIENT

Active Ingredients: Apis regina (Queen Bee cell with larva and nutrient fluid) 6X, Argentum met. (Silver) 6X, Testes (Bovine testes) 6X

Inactive Ingredients: Water, Salt, Lactose

PURPOSE

Use: Temporary relief of headache.

KEEP OUT OF REACH OF CHILDREN.

WARNINGS

Warnings: Claims based on traditional homeopathic practice, not accepted medical evidence. Not FDA evaluated. Do not use if allergic to any ingredient. Consult a doctor before use for serious conditions or if conditions worsen or persist. If pregnant or nursing, consult a doctor before use.

QUESTIONS

Questions? Call 866.642.2858 Uriel, East Troy, WI 53120 shopuriel.com